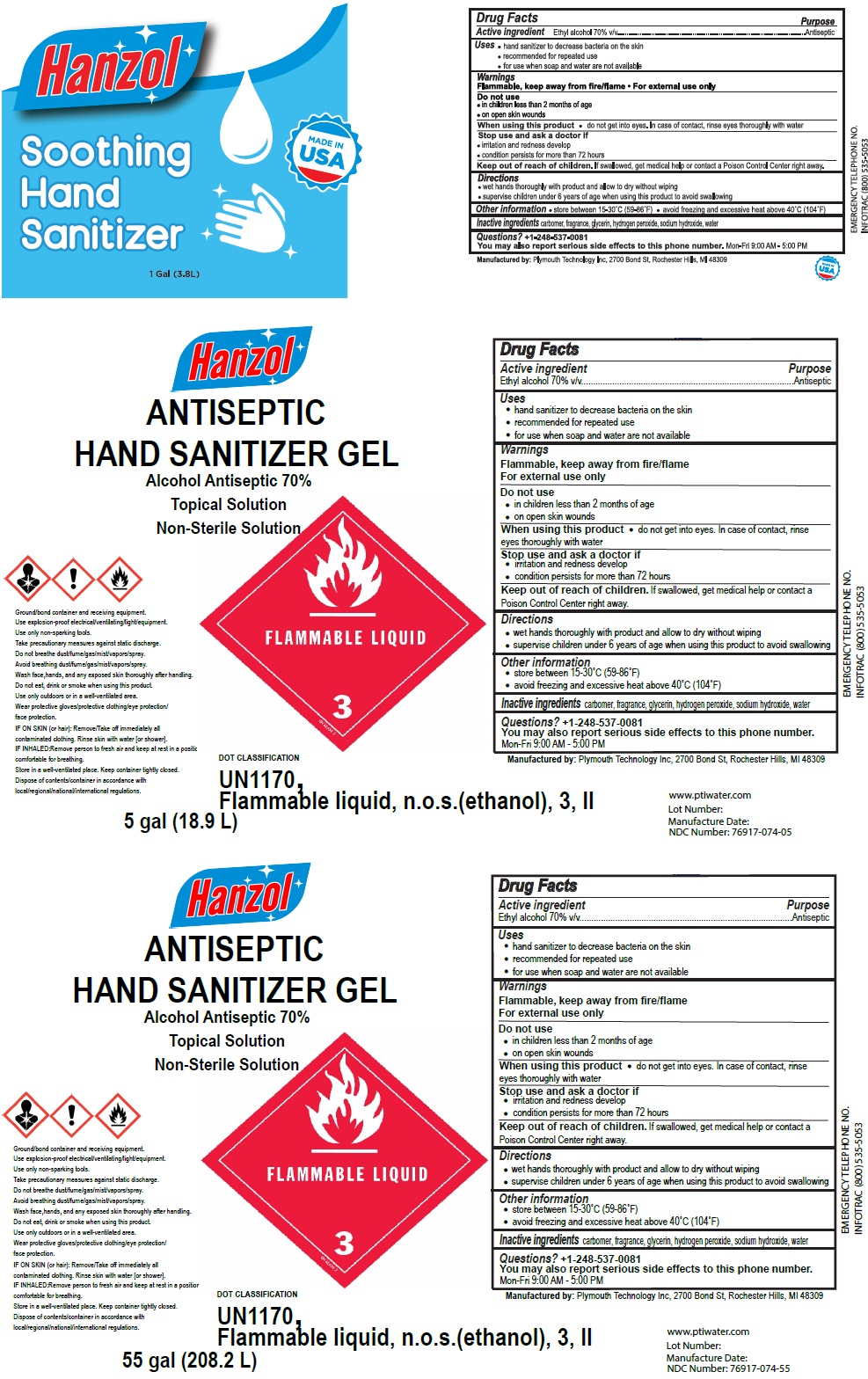 DRUG LABEL: Hanzol
NDC: 76917-074 | Form: GEL
Manufacturer: Plymouth Technology, Inc.
Category: otc | Type: HUMAN OTC DRUG LABEL
Date: 20200522

ACTIVE INGREDIENTS: ALCOHOL 70 L/100 L
INACTIVE INGREDIENTS: CARBOMER HOMOPOLYMER, UNSPECIFIED TYPE; GLYCERIN; HYDROGEN PEROXIDE; SODIUM HYDROXIDE; WATER

Hanzol Antiseptic Hand Sanitizer Gel

Active ingredient

Ethyl alcohol 70% v/v

Purpose

Antiseptic

Uses

• hand sanitizer to decrease bacteria on the skin

• recommended for repeated use

• for use when soap and water are not available

Warnings

Flammable, keep away from fire/flame

For external use only

Do not use

• in children less than 2 months of age

• on open skin wounds

When using this product • do not get into eyes. In case of contact, rinse eyes thoroughly with water.

Stop use and ask a doctor if

• irritation and redness develop

• condition persists for more than 72 hours

Keep out of reach of children. If swallowed, get medical help or contact a Poison Control Center right away.

Directions

• wet hands thoroughly with product and allow to dry without wiping

• supervise children under 6 years of age when using this product to avoid swallowing

Other information

• store between 15-30° C (59-86° F)

• avoid freezing and excessive heat above 40° C (104°F)

INACTIVE INGREDIENT

Inactive ingredients carbomer, fragrance, glycerin, hydrogen peroxide, sodium hydroxide, water

Questions? 1-248-537-0081

You may also report serious side effects to this phone number.

Mon- Fri 9:00AM - 5.00PM

Alcohol Antiseptic 70%

Topical Solution

Non-Sterile Solution

FLAMMABLE LIQUID

Ground/bond container and receiving equipment.

Use explosion-proof electrical/ventilating/light/equipment.

Use only non-sparking tools.

Take precautionary measures against static discharge.

Do not breathe dust/fume/gas/mist/vapors/spray.

Avoid breathing dust/fume/gas/mist/vapors/spray.

Wash face,hands, and any exposed skin thoroughly after handling.

Do not eat, drink or smoke when using this product.

Use only outdoors or in a well-ventilated area.

Wear protective gloves/protective clothing/eye protection/face protection

IF ON SKIN (or hair): Remove/Take off immediately all contaminated clothing. Rinse skin with water [or shower].

IF INHALED:Remove person to fresh air and keep at rest in a position comfortable for breathing.

Store in a well-ventilated place. Keep container tightly closed.

Dispose of contents/container in accordance with local/regional/national/international regulations.

DOT CLASSIFICATION

UN1170, Flammable liquid, n.o.s.(ethanol), 3, II Lot Number:

MADE IN USA

Manufactured by: Plymouth Technology, Inc, 2700 Bond St, Rochester Hills, MI 48309

EMERGENCY TELEPHONE NO.

INFOTRAC (800) 535-5053

www.ptiwater.com